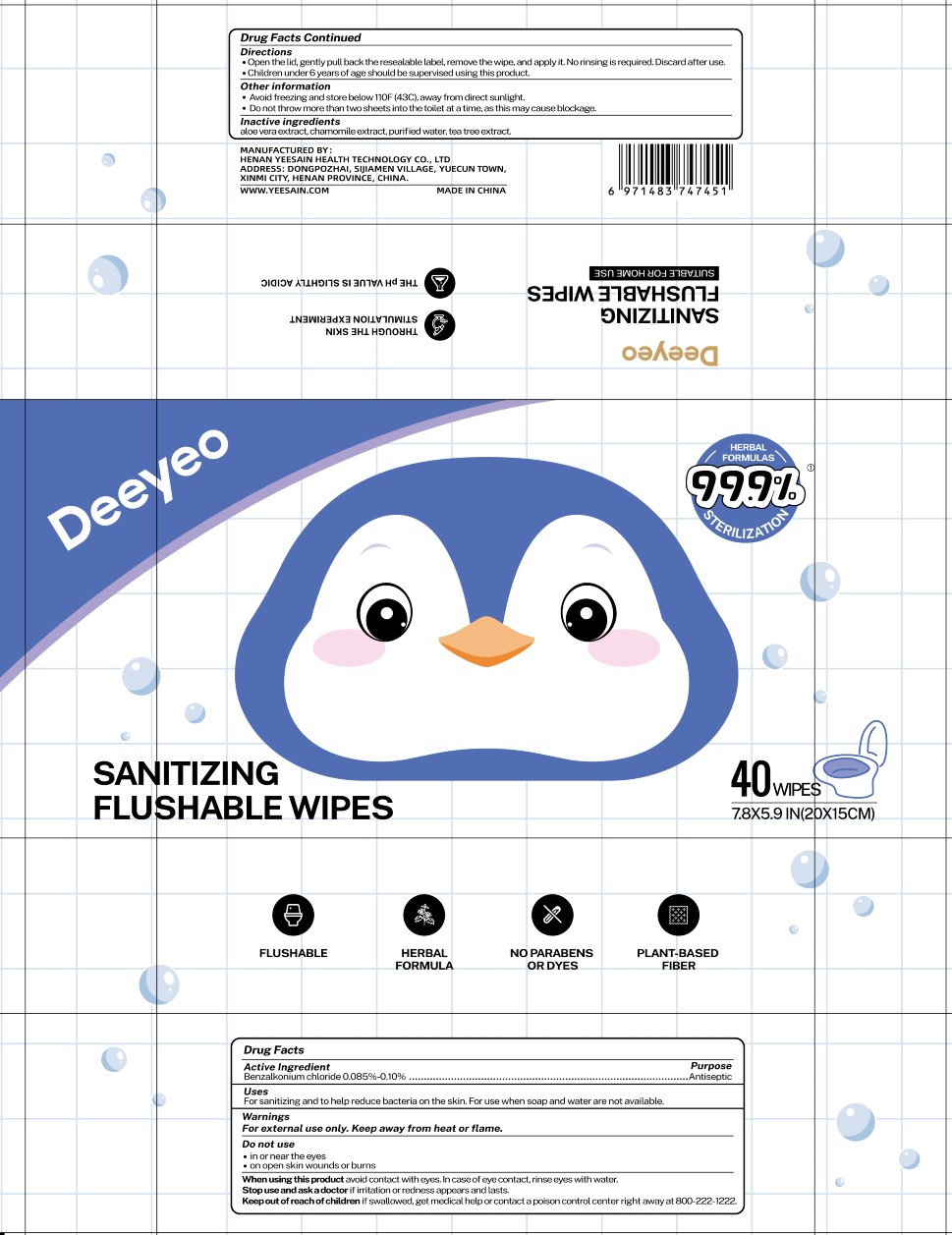 DRUG LABEL: DEEYEO
NDC: 75622-655 | Form: CLOTH
Manufacturer: Henan Yeesain Health Technology Co., Ltd.
Category: otc | Type: HUMAN OTC DRUG LABEL
Date: 20241227

ACTIVE INGREDIENTS: BENZALKONIUM CHLORIDE 0.13 mg/100 mL
INACTIVE INGREDIENTS: ALOE VERA LEAF; TEA TREE OIL; CHAMOMILE; WATER

BZK Wipe Deeyeo

Active Ingredient(s)

Benzalkonium chloride 0.13%

Purpose

Antiseptic

Use

For sanitizing and to help reduce bacteria on the skin. For use when soap and water are not available.

Warnings

For external use only. Keep away from heat or flame

Do not use

- in or near the eyes.
- on open skin wounds or burns

KEEP OUT OF REACH OF CHILDREN

Keep children out of reach unless under adult supervision. If swallowed, get medical help or contact a poison control center right away

Directions

Open lid, gently pull back resealable label, remove, and apply to hands and skin.
No rinsing required. Discard after use.

Children under 6 years of age should be supervised when using this product.

Other information

Avoid freezing and store below 110F (43C), away from direct sunlight.

May discolor certain fabrics or surfaces.

Inactive ingredients

water, flushable non-woven fabric, tea tree extract, chamomile extract, aloe vera extract

Package Label - Principal Display Panel

40 PCS, NDC: 75622-655-40